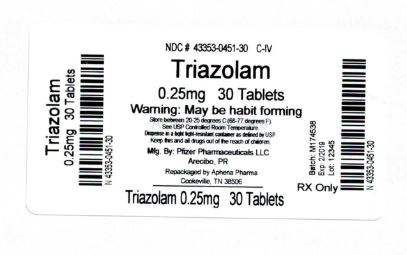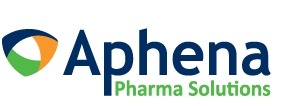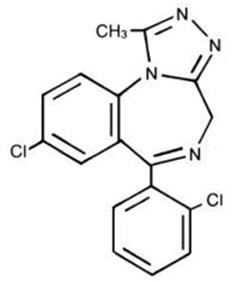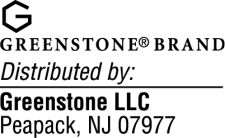 DRUG LABEL: Triazolam
NDC: 43353-451 | Form: TABLET
Manufacturer: Aphena Pharma Solutions - Tennessee, LLC
Category: prescription | Type: HUMAN PRESCRIPTION DRUG LABEL
Date: 20171116
DEA Schedule: CIV

ACTIVE INGREDIENTS: TRIAZOLAM 0.25 mg/1 1
INACTIVE INGREDIENTS: POWDERED CELLULOSE; STARCH, CORN; DOCUSATE SODIUM; FD&C BLUE NO. 2; LACTOSE, UNSPECIFIED FORM; MAGNESIUM STEARATE; SILICON DIOXIDE; SODIUM BENZOATE

Triazolam tablets, USP CIV

WARNING: RISKS FROM CONCOMITANT USE WITH OPIOIDS

Concomitant use of benzodiazepines and opioids may result in profound sedation, respiratory depression, coma, and death [see Warnings, Drug Interactions].

- Reserve concomitant prescribing of these drugs for use in patients for whom alternative treatment options are inadequate.
- Limit dosages and durations to the minimum required.
  Follow patients for signs and symptoms of respiratory depression and sedation.

DESCRIPTION

Triazolam is a triazolobenzodiazepine hypnotic agent.

Triazolam is a white crystalline powder, soluble in alcohol and poorly soluble in water. It has a molecular weight of 343.21.

The chemical name for triazolam is 8-chloro-6-(o-chlorophenyl)-1-methyl-4H-s-triazolo-[4,3-α] [1,4] benzodiazepine.

The structural formula is represented below:

Each triazolam tablet, for oral administration, contains 0.125 mg or 0.25 mg of triazolam. Inactive ingredients: 0.125 mg—cellulose, corn starch, docusate sodium, lactose, magnesium stearate, silicon dioxide, sodium benzoate; 0.25 mg—cellulose, corn starch, docusate sodium, FD&C Blue No. 2, lactose, magnesium stearate, silicon dioxide, sodium benzoate.

CLINICAL PHARMACOLOGY

Triazolam is a hypnotic with a short mean plasma half-life reported to be in the range of 1.5 to 5.5 hours. In normal subjects treated for 7 days with four times the recommended dosage, there was no evidence of altered systemic bioavailability, rate of elimination, or accumulation. Peak plasma levels are reached within 2 hours following oral administration. Following recommended doses of triazolam tablets, triazolam peak plasma levels in the range of 1 to 6 ng/mL are seen. The plasma levels achieved are proportional to the dose given.

Triazolam and its metabolites, principally as conjugated glucuronides, which are presumably inactive, are excreted primarily in the urine. Only small amounts of unmetabolized triazolam appear in the urine. The two primary metabolites accounted for 79.9% of urinary excretion. Urinary excretion appeared to be biphasic in its time course.

Triazolam tablets 0.5 mg, in two separate studies, did not affect the prothrombin times or plasma warfarin levels in male volunteers administered sodium warfarin orally.

Extremely high concentrations of triazolam do not displace bilirubin bound to human serum albumin in vitro.

Triazolam ^14C was administered orally to pregnant mice. Drug-related material appeared uniformly distributed in the fetus with ^14C concentrations approximately the same as in the brain of the mother.

In sleep laboratory studies, triazolam tablets significantly decreased sleep latency, increased the duration of sleep, and decreased the number of nocturnal awakenings. After 2 weeks of consecutive nightly administration, the drug's effect on total wake time is decreased, and the values recorded in the last third of the night approach baseline levels. On the first and/or second night after drug discontinuance (first or second post-drug night), total time asleep, percentage of time spent sleeping, and rapidity of falling asleep frequently were significantly less than on baseline (predrug) nights. This effect is often called "rebound" insomnia.

The type and duration of hypnotic effects and the profile of unwanted effects during administration of benzodiazepine drugs may be influenced by the biologic half-life of administered drug and any active metabolites formed. When half-lives are long, the drug or metabolites may accumulate during periods of nightly administration and be associated with impairments of cognitive and motor performance during waking hours; the possibility of interaction with other psychoactive drugs or alcohol will be enhanced. In contrast, if half-lives are short, the drug and metabolites will be cleared before the next dose is ingested, and carry-over effects related to excessive sedation or CNS depression should be minimal or absent. However, during nightly use for an extended period pharmacodynamic tolerance or adaptation to some effects of benzodiazepine hypnotics may develop. If the drug has a short half-life of elimination, it is possible that a relative deficiency of the drug or its active metabolites (ie, in relationship to the receptor site) may occur at some point in the interval between each night's use. This sequence of events may account for two clinical findings reported to occur after several weeks of nightly use of rapidly eliminated benzodiazepine hypnotics: 1) increased wakefulness during the last third of the night and 2) the appearance of increased daytime anxiety after 10 days of continuous treatment.

In a study of elderly (62–83 years old) versus younger subjects (21–41 years old) who received triazolam at the same dose levels (0.125 mg and 0.25 mg), the elderly experienced both greater sedation and impairment of psychomotor performance. These effects resulted largely from higher plasma concentrations of triazolam in the elderly.

INDICATIONS AND USAGE

Triazolam is indicated for the short-term treatment of insomnia (generally 7–10 days). Use for more than 2–3 weeks requires complete reevaluation of the patient (see WARNINGS).

Prescriptions for triazolam should be written for short-term use (7–10 days) and it should not be prescribed in quantities exceeding a 1-month supply.

CONTRAINDICATIONS

Triazolam tablets are contraindicated in patients with known hypersensitivity to this drug or other benzodiazepines.

Benzodiazepines may cause fetal damage when administered during pregnancy. An increased risk of congenital malformations associated with the use of diazepam and chlordiazepoxide during the first trimester of pregnancy has been suggested in several studies. Transplacental distribution has resulted in neonatal CNS depression following the ingestion of therapeutic doses of a benzodiazepine hypnotic during the last weeks of pregnancy.

Triazolam is contraindicated in pregnant women. If there is a likelihood of the patient becoming pregnant while receiving triazolam, she should be warned of the potential risk to the fetus. Patients should be instructed to discontinue the drug prior to becoming pregnant. The possibility that a woman of childbearing potential may be pregnant at the time of institution of therapy should be considered.

Triazolam is contraindicated with medications that significantly impair the oxidative metabolism mediated by cytochrome P450 3A (CYP 3A) including ketoconazole, itraconazole, nefazodone, and several HIV protease inhibitors, (see WARNINGS and PRECAUTIONS–Drug Interactions).

WARNINGS

Risks from Concomitant Use with Opioids

Concomitant use of benzodiazepines, including triazolam, and opioids may result in profound sedation, respiratory depression, coma, and death. Because of these risks, reserve concomitant prescribing of these drugs for use in patients for whom alternative treatment options are inadequate.

Observational studies have demonstrated that concomitant use of opioid analgesics and benzodiazepines increases the risk of drug-related mortality compared to use of opioids alone. If a decision is made to prescribe triazolam concomitantly with opioids, prescribe the lowest effective dosages and minimum durations of concomitant use, and follow patients closely for signs and symptoms of respiratory depression and sedation. In patients already receiving an opioid analgesic, prescribe a lower initial dose of triazolam than indicated in the absence of an opioid and titrate based on clinical response. If an opioid is initiated in a patient already taking triazolam, prescribe a lower initial dose of the opioid and titrate based upon clinical response.

Advise both patients and caregivers about the risks of respiratory depression and sedation when triazolam is used with opioids. Advise patients not to drive or operate heavy machinery until the effects of concomitant use with the opioid have been determined [see Drug Interactions].

Persistent or Worsening Insomnia

Because sleep disturbances may be the presenting manifestation of a physical and/or psychiatric disorder, symptomatic treatment of insomnia should be initiated only after a careful evaluation of the patient. The failure of insomnia to remit after 7 to 10 days of treatment may indicate the presence of a primary psychiatric and/or medical illness that should be evaluated. Worsening of insomnia or the emergence of new thinking or behavior abnormalities may be the consequence of an unrecognized psychiatric or physical disorder. Such findings have emerged during the course of treatment with sedative-hypnotic drugs. Because some of the important adverse effects of sedative-hypnotics appear to be dose related (see Precautions and Dosage and Administration), it is important to use the smallest possible effective dose, especially in the elderly.

"Sleep-driving" and Other Complex Behaviors

Complex behaviors such as "sleep-driving" (i.e., driving while not fully awake after ingestion of a sedative-hypnotic, with amnesia for the event) have been reported. These events can occur in sedative-hypnotic-naïve as well as in sedative-hypnotic-experienced persons. Although behaviors such as sleep-driving may occur with sedative-hypnotics alone at therapeutic doses, the use of alcohol and other CNS depressants with sedative-hypnotics appears to increase the risk of such behaviors, as does the use of sedative-hypnotics at doses exceeding the maximum recommended dose. Due to the risk to the patient and the community, discontinuation of sedative-hypnotics should be strongly considered for patients who report a "sleep-driving" episode.

Other complex behaviors (e.g., preparing and eating food, making phone calls, or having sex) have been reported in patients who are not fully awake after taking a sedative-hypnotic. As with sleep-driving, patients usually do not remember these events.

Severe anaphylactic and anaphylactoid reactions

Rare cases of angioedema involving the tongue, glottis or larynx have been reported in patients after taking the first or subsequent doses of sedative-hypnotics, including triazolam. Some patients have had additional symptoms such as dyspnea, throat closing, or nausea and vomiting that suggest anaphylaxis. Some patients have required medical therapy in the emergency department. If angioedema involves the tongue, glottis or larynx, airway obstruction may occur and be fatal. Patients who develop angioedema after treatment with triazolam should not be rechallenged with the drug.

Central nervous system manifestations

An increase in daytime anxiety has been reported for triazolam after as few as 10 days of continuous use. In some patients this may be a manifestation of interdose withdrawal (see CLINICAL PHARMACOLOGY). If increased daytime anxiety is observed during treatment, discontinuation of treatment may be advisable.

A variety of abnormal thinking and behavior changes have been reported to occur in association with the use of benzodiazepine hypnotics including triazolam. Some of these changes may be characterized by decreased inhibition, eg, aggressiveness and extroversion that seem excessive, similar to that seen with alcohol and other CNS depressants (eg, sedative/hypnotics). Other kinds of behavioral changes have also been reported, for example, bizarre behavior, agitation, hallucinations, depersonalization. In primarily depressed patients, the worsening of depression, including suicidal thinking, has been reported in association with the use of benzodiazepines.

It can rarely be determined with certainty whether a particular instance of the abnormal behaviors listed above is drug induced, spontaneous in origin, or a result of an underlying psychiatric or physical disorder. Nonetheless, the emergence of any new behavioral sign or symptom of concern requires careful and immediate evaluation.

Because of its depressant CNS effects, patients receiving triazolam should be cautioned against engaging in hazardous occupations requiring complete mental alertness such as operating machinery or driving a motor vehicle. For the same reason, patients should be cautioned about the concomitant ingestion of alcohol and other CNS depressant drugs during treatment with triazolam tablets.

As with some, but not all benzodiazepines, anterograde amnesia of varying severity and paradoxical reactions have been reported following therapeutic doses of triazolam. Data from several sources suggest that anterograde amnesia may occur at a higher rate with triazolam than with other benzodiazepine hypnotics.

Triazolam interaction with drugs that inhibit metabolism via cytochrome P450 3A

The initial step in triazolam metabolism is hydroxylation catalyzed by cytochrome P450 3A (CYP 3A). Drugs that inhibit this metabolic pathway may have a profound effect on the clearance of triazolam. Consequently, triazolam should be avoided in patients receiving very potent inhibitors of CYP 3A. With drugs inhibiting CYP 3A to a lesser but still significant degree, triazolam should be used only with caution and consideration of appropriate dosage reduction. For some drugs, an interaction with triazolam has been quantified with clinical data; for other drugs, interactions are predicted from in vitro data and/or experience with similar drugs in the same pharmacologic class.

The following are examples of drugs known to inhibit the metabolism of triazolam and/or related benzodiazepines, presumably through inhibition of CYP 3A.

Potent CYP 3A inhibitors

Potent inhibitors of CYP 3A that should not be used concomitantly with triazolam include ketoconazole, itraconazole, nefazodone and several HIV protease inhibitors including ritonavir, indinavir, nelfinavir, saquinavir and lopinavir. Although data concerning the effects of azole-type antifungal agents other than ketoconazole and itraconazole on triazolam metabolism are not available, they should be considered potent CYP 3A inhibitors, and their coadministration with triazolam is not recommended (see CONTRAINDICATIONS).

Drugs demonstrated to be CYP 3A inhibitors on the basis of clinical studies involving triazolam (caution and consideration of dose reduction are recommended during coadministration with triazolam)

Macrolide Antibiotics

Coadministration of erythromycin increased the maximum plasma concentration of triazolam by 46%, decreased clearance by 53%, and increased half-life by 35%; caution and consideration of appropriate triazolam dose reduction are recommended. Similar caution should be observed during coadministration with clarithromycin and other macrolide antibiotics.

Cimetidine

Coadministration of cimetidine increased the maximum plasma concentration of triazolam by 51%, decreased clearance by 55%, and increased half-life by 68%; caution and consideration of appropriate triazolam dose reduction are recommended.

Other drugs possibly affecting triazolam metabolism by inhibition of CYP 3A are discussed in the PRECAUTIONS section (see PRECAUTIONS–Drug Interactions).

PRECAUTIONS

General

In elderly and/or debilitated patients it is recommended that treatment with triazolam tablets be initiated at 0.125 mg to decrease the possibility of development of oversedation, dizziness, or impaired coordination.

Some side effects reported in association with the use of triazolam appear to be dose related. These include drowsiness, dizziness, light-headedness, and amnesia.

The relationship between dose and what may be more serious behavioral phenomena is less certain. Specifically, some evidence, based on spontaneous marketing reports, suggests that confusion, bizarre or abnormal behavior, agitation, and hallucinations may also be dose related, but this evidence is inconclusive. In accordance with good medical practice it is recommended that therapy be initiated at the lowest effective dose (see DOSAGE AND ADMINISTRATION).

Cases of "traveler's amnesia" have been reported by individuals who have taken triazolam to induce sleep while traveling, such as during an airplane flight. In some of these cases, insufficient time was allowed for the sleep period prior to awakening and before beginning activity. Also, the concomitant use of alcohol may have been a factor in some cases.

Caution should be exercised if triazolam is prescribed to patients with signs or symptoms of depression that could be intensified by hypnotic drugs. Suicidal tendencies may be present in such patients and protective measures may be required. Intentional over-dosage is more common in these patients, and the least amount of drug that is feasible should be available to the patient at any one time.

The usual precautions should be observed in patients with impaired renal or hepatic function, chronic pulmonary insufficiency, and sleep apnea. In patients with compromised respiratory function, respiratory depression and apnea have been reported infrequently.

Information for patients

The text of a Medication Guide for patients is included at the end of this insert. To assure safe and effective use of triazolam, the information and instructions provided in this Medication Guide should be discussed with patients.

Risks from Concomitant Use with Opioids

Advise both patients and caregivers about the risks of potentially fatal respiratory depression and sedation when triazolam is used with opioids and not to use such drugs concomitantly unless supervised by a healthcare provider. Advise patients not to drive or operate heavy machinery until the effects of concomitant use with the opioid have been determined [see Drug Interactions].

"Sleep-driving" and other complex behaviors

There have been reports of people getting out of bed after taking a sedative-hypnotic and driving their cars while not fully awake, often with no memory of the event. If a patient experiences such an episode, it should be reported to his or her doctor immediately, since "sleep-driving" can be dangerous. This behavior is more likely to occur when sedative-hypnotics are taken with alcohol or other central nervous system depressants (see WARNINGS). Other complex behaviors (e.g., preparing and eating food, making phone calls, or having sex) have been reported in patients who are not fully awake after taking a sedative hypnotic. As with sleep-driving, patients usually do not remember these events.

Laboratory tests

Laboratory tests are not ordinarily required in otherwise healthy patients.

Drug interactions

The concomitant use of benzodiazepines and opioids increases the risk of respiratory depression because of actions at different receptor sites in the CNS that control respiration. Benzodiazepines interact at GABAA sites and opioids interact primarily at mu receptors. When benzodiazepines and opioids are combined, the potential for benzodiazepines to significantly worsen opioid-related respiratory depression exists. Limit dosage and duration of concomitant use of benzodiazepines and opioids, and monitor patients closely for respiratory depression and sedation.

Both pharmacodynamic and pharmacokinetic interactions have been reported with benzodiazepines. In particular, triazolam produces additive CNS depressant effects when coadministered with other psychotropic medications, anticonvulsants, antihistamines, ethanol, and other drugs which themselves produce CNS depression.

Drugs that inhibit triazolam metabolism via cytochrome P450 3A

The initial step in triazolam metabolism is hydroxylation catalyzed by cytochrome P450 3A (CYP 3A). Drugs which inhibit this metabolic pathway may have a profound effect on the clearance of triazolam (see CONTRAINDICATIONS and WARNINGS for additional drugs of this type). Triazolam is contraindicated with ketoconzaole, itraconazole, nefazodone, and several HIV protease inhibitors.

Drugs and other substances demonstrated to be CYP 3A inhibitors of possible clinical significance on the basis of clinical studies involving triazolam (caution is recommended during coadministration with triazolam)

Isoniazid

Coadministration of isoniazid increased the maximum plasma concentration of triazolam by 20%, decreased clearance by 42%, and increased half-life by 31%.

Oral contraceptives

Coadministration of oral contraceptives increased maximum plasma concentration by 6%, decreased clearance by 32%, and increased half-life by 16%.

Grapefruit juice

Coadministration of grapefruit juice increased the maximum plasma concentration of triazolam by 25%, increased the area under the concentration curve by 48%, and increased half-life by 18%.

Drugs demonstrated to be CYP 3A inhibitors on the basis of clinical studies involving benzodiazepines metabolized similarly to triazolam or on the basis of in vitro studies with triazolam or other benzodiazepines (caution is recommended during coadministration with triazolam)

Available data from clinical studies of benzodiazepines other than triazolam suggest a possible drug interaction with triazolam for the following: fluvoxamine, diltiazem, and verapamil. Data from in vitro studies of triazolam suggest a possible drug interaction with triazolam for the following: sertraline and paroxetine. Data from in vitro studies of benzodiazepines other than triazolam suggest a possible drug interaction with triazolam for the following: ergotamine, cyclosporine, amiodarone, nicardipine, and nifedipine. Caution is recommended during coadministration of any of these drugs with triazolam (see WARNINGS).

Drugs that affect triazolam pharmacokinetics by other mechanisms

Ranitidine

Coadministration of ranitidine increased the maximum plasma concentration of triazolam by 30%, increased the area under the concentration curve by 27%, and increased half-life by 3.3%. Caution is recommended during coadministration with triazolam.

Carcinogenesis, mutagenesis, impairment of fertility

No evidence of carcinogenic potential was observed in mice during a 24-month study with triazolam in doses up to 4,000 times the human dose.

Pregnancy

1. Teratogenic effects

Pregnancy category X (see CONTRAINDICATIONS).

2. Non-teratogenic effects

It is to be considered that the child born of a mother who is on benzodiazepines may be at some risk for withdrawal symptoms from the drug, during the postnatal period. Also, neonatal flaccidity has been reported in an infant born of a mother who had been receiving benzodiazepines.

Nursing mothers

Human studies have not been performed; however, studies in rats have indicated that triazolam and its metabolites are secreted in milk. Therefore, administration of triazolam to nursing mothers is not recommended.

Pediatric use

Safety and effectiveness of triazolam in individuals below 18 years of age have not been established.

Geriatric use

The elderly are especially susceptible to the dose related adverse effects of triazolam. They exhibit higher plasma triazolam concentrations due to reduced clearance of the drug as compared with younger subjects at the same dose. To minimize the possibility of development of oversedation, the smallest effective dose should be used (see CLINICAL PHARMACOLOGY, WARNINGS, PRECAUTIONS, and DOSAGE AND ADMINISTRATION).

Tolerance/Withdrawal Phenomena

Some loss of effectiveness or adaptation to the sleep inducing effects of these medications may develop after nightly use for more than a few weeks and there may be a degree of dependence that develops. For the benzodiazepine sleeping pills that are eliminated quickly from the body, a relative deficiency of the drug may occur at some point in the interval between each night's use. This can lead to (1) increased wakefulness during the last third of the night, and (2) the appearance of increased signs of daytime anxiety or nervousness. These two events have been reported in particular for triazolam.

There can be more severe 'withdrawal' effects when a benzodiazepine sleeping pill is stopped. Such effects can occur after discontinuing these drugs following use for only a week or two, but may be more common and more severe after longer periods of continuous use. One type of withdrawal phenomenon is the occurrence of what is known as 'rebound insomnia'. That is, on the first few nights after the drug is stopped, insomnia is actually worse than before the sleeping pill was given. Other withdrawal phenomena following abrupt stopping of benzodiazepine sleeping pills range from mild unpleasant feelings to a major withdrawal syndrome which may include abdominal and muscle cramps, vomiting, sweating, tremor, and rarely, convulsions.

ADVERSE REACTIONS

During placebo-controlled clinical studies in which 1,003 patients received triazolam tablets, the most troublesome side effects were extensions of the pharmacologic activity of triazolam, eg, drowsiness, dizziness, or light-headedness.

The figures cited below are estimates of untoward clinical event incidence among subjects who participated in the relatively short duration (i.e., 1 to 42 days) placebo-controlled clinical trials of triazolam. The figures cannot be used to predict precisely the incidence of untoward events in the course of usual medical practice where patient characteristics and other factors often differ from those in clinical trials. These figures cannot be compared with those obtained from other clinical studies involving related drug products and placebo, as each group of drug trials is conducted under a different set of conditions.

Comparison of the cited figures, however, can provide the prescriber with some basis for estimating the relative contributions of drug and nondrug factors to the untoward event incidence rate in the population studied. Even this use must be approached cautiously, as a drug may relieve a symptom in one patient while inducing it in others. (For example, an anticholinergic, anxiolytic drug may relieve dry mouth [a sign of anxiety] in some subjects but induce it [an untoward event] in others.)

 | Triazolam | PLACEBO
Number of Patients | 1003 | 997
% Patients Reporting:
Central Nervous System
Drowsiness | 14.0 | 6.4
Headache | 9.7 | 8.4
Dizziness | 7.8 | 3.1
Nervousness | 5.2 | 4.5
Light-headedness | 4.9 | 0.9
Coordination disorders/ataxia | 4.6 | 0.8
Gastrointestinal
Nausea/vomiting | 4.6 | 3.7

In addition to the relatively common (i.e., 1% or greater) untoward events enumerated above, the following adverse events have been reported less frequently (i.e., 0.9% to0.5%): euphoria, tachycardia, tiredness, confusional states/memory impairment, cramps/pain, depression, visual disturbances.

Rare (i.e., less than 0.5%) adverse reactions included constipation, taste alterations, diarrhea, dry mouth, dermatitis/allergy, dreaming/nightmares, insomnia, paresthesia, tinnitus, dysesthesia, weakness, congestion, death from hepatic failure in a patient also receiving diuretic drugs.

In addition to these untoward events for which estimates of incidence are available, the following adverse events have been reported in association with the use of triazolam and other benzodiazepines: amnestic symptoms (anterograde amnesia with appropriate or inappropriate behavior), confusional states (disorientation, derealization, depersonalization, and/or clouding of consciousness), dystonia, anorexia, fatigue, sedation, slurred speech, jaundice, pruritus, dysarthria, changes in libido, menstrual irregularities, incontinence, and urinary retention. Other factors may contribute to some of these reactions, eg, concomitant intake of alcohol or other drugs, sleep deprivation, an abnormal premorbid state, etc.

Other events reported include: paradoxical reactions such as stimulation, mania, an agitational state (restlessness, irritability, and excitation), increased muscle spasticity, sleep disturbances, hallucinations, delusions, aggressiveness, falling, somnambulism, syncope, inappropriate behavior and other adverse behavioral effects. Should these occur, use of the drug should be discontinued.

The following events have also been reported: chest pain, burning tongue/glossitis/stomatitis.

Laboratory analyses were performed on all patients participating in the clinical program for triazolam. The following incidences of abnormalities were observed in patients receiving triazolam and the corresponding placebo group. None of these changes were considered to be of physiological significance.

 | Triazolam |  | PLACEBO
Number of Patients | 380 |  | 361
% of Patients Reporting: | Low | High | Low | High
Hematology
Hematocrit | [Less than 1%]
Hemoglobin
Total WBC count | 1.7 | 2.1 |  | 1.3
Neutrophil count | 1.5 | 1.5 | 3.3 | 1.0
Lymphocyte count | 2.3 | 4.0 | 3.1 | 3.8
Monocyte count | 3.6 |  | 4.4 | 1.5
Eosinophil count | 10.2 | 3.2 | 9.8 | 3.4
Basophil count | 1.7 | 2.1 |  | 1.8
Urinalysis
Albumin | — | 1.1 | —
Sugar | — |  | —
RBC/HPF | — | 2.9 | — | 2.9
WBC/HPF | — | 11.7 | — | 7.9
Blood chemistry
Creatinine | 2.4 | 1.9 | 3.6 | 1.5
Bilirubin |  | 1.5 | 1.0
SGOT |  | 5.3 |  | 4.5
Alkaline phosphatase |  | 2.2 |  | 2.6

When treatment with triazolam is protracted, periodic blood counts, urinalysis, and blood chemistry analyses are advisable.

Minor changes in EEG patterns, usually low-voltage fast activity, have been observed in patients during therapy with triazolam and are of no known significance.

DRUG ABUSE AND DEPENDENCE

Abuse and addiction are separate and distinct from physical dependence and tolerance. Abuse is characterized by misuse of the drug for non-medical purposes, often in combination with other psychoactive substances. Physical dependence is a state of adaptation that is manifested by a specific withdrawal syndrome that can be produced by abrupt cessation, rapid dose reduction, decreasing blood level of the drug and/or administration of an antagonist. Tolerance is a state of adaptation in which exposure to a drug induces changes that result in a diminution of one or more of the drug's effects over time. Tolerance may occur to both the desired and undesired effects of drugs and may develop at different rates for different effects.

Addiction is a primary, chronic, neurobiological disease with genetic, psychosocial, and environmental factors influencing its development and manifestations. It is characterized by behaviors that include one or more of the following: impaired control over drug use, compulsive use, continued use despite harm, and craving. Drug addiction is a treatable disease, utilizing a multidisciplinary approach, but relapse is common.

Controlled Substance

Triazolam is a controlled substance under the Controlled Substance Act, and triazolam tablets have been assigned to Schedule IV.

Abuse, Dependence and Withdrawal

Withdrawal symptoms, similar in character to those noted with barbiturates and alcohol (convulsions, tremor, abdominal and muscle cramps, vomiting, sweating, dysphoria, perceptual disturbances and insomnia), have occurred following abrupt discontinuance of benzodiazepines, including triazolam. The more severe symptoms are usually associated with higher dosages and longer usage, although patients at therapeutic dosages given for as few as 1–2 weeks can also have withdrawal symptoms and in some patients there may be withdrawal symptoms (daytime anxiety, agitation) between nightly doses (see CLINICAL PHARMACOLOGY). Consequently, abrupt discontinuation should be avoided and a gradual dosage tapering schedule is recommended in any patient taking more than the lowest dose for more than a few weeks. The recommendation for tapering is particularly important in any patient with a history of seizure.

The risk of dependence is increased in patients with a history of alcoholism, drug abuse, or in patients with marked personality disorders. Such dependence-prone individuals should be under careful surveillance when receiving triazolam. As with all hypnotics, repeat prescriptions should be limited to those who are under medical supervision.

OVERDOSAGE

Because of the potency of triazolam, some manifestations of overdosage may occur at 2 mg, four times the maximum recommended therapeutic dose (0.5 mg).

Manifestations of overdosage with triazolam tablets include somnolence, confusion, impaired coordination, slurred speech, and ultimately, coma. Respiratory depression and apnea have been reported with overdosages of triazolam. Seizures have occasionally been reported after overdosages.

Death has been reported in association with overdoses of triazolam by itself, as it has with other benzodiazepines. In addition, fatalities have been reported in patients who have overdosed with a combination of a single benzodiazepine, including triazolam, and alcohol; benzodiazepine and alcohol levels seen in some of these cases have been lower than those usually associated with reports of fatality with either substance alone.

As in all cases of drug overdosage, respiration, pulse, and blood pressure should be monitored and supported by general measures when necessary. Immediate gastric lavage should be performed. An adequate airway should be maintained. Intravenous fluids may be administered.

Flumazenil, a specific benzodiazepine receptor antagonist, is indicated for the complete or partial reversal of the sedative effects of benzodiazepines and may be used in situations when an overdose with a benzodiazepine is known or suspected. Prior to the administration of flumazenil, necessary measures should be instituted to secure airway, ventilation and intravenous access. Flumazenil is intended as an adjunct to, not as a substitute for, proper management of benzodiazepine overdose. Patients treated with flumazenil should be monitored for resedation, respiratory depression, and other residual benzodiazepine effects for an appropriate period after treatment. The prescriber should be aware of a risk of seizure in association with flumazenil treatment, particularly in long-term benzodiazepine users and in cyclic antidepressant overdose. The complete flumazenil package insert including CONTRAINDICATIONS, WARNINGS and PRECAUTIONS should be consulted prior to use.

Experiments in animals have indicated that cardiopulmonary collapse can occur with massive intravenous doses of triazolam. This could be reversed with positive mechanical respiration and the intravenous infusion of norepinephrine bitartrate or metaraminol bitartrate. Hemodialysis and forced diuresis are probably of little value. As with the management of intentional overdosage with any drug, the physician should bear in mind that multiple agents may have been ingested by the patient.

The oral LD50 in mice is greater than 1,000 mg/kg and in rats is greater than 5,000 mg/kg.

DOSAGE AND ADMINISTRATION

It is important to individualize the dosage of triazolam tablets for maximum beneficial effect and to help avoid significant adverse effects.

The recommended dose for most adults is 0.25 mg before retiring. A dose of 0.125 mg may be found to be sufficient for some patients (e.g., low body weight). A dose of 0.5 mg should be used only for exceptional patients who do not respond adequately to a trial of a lower dose since the risk of several adverse reactions increases with the size of the dose administered. A dose of 0.5 mg should not be exceeded.

In geriatric and/or debilitated patients the recommended dosage range is 0.125 mg to 0.25 mg. Therapy should be initiated at 0.125 mg in these groups and the 0.25 mg dose should be used only for exceptional patients who do not respond to a trial of the lower dose. A dose of 0.25 mg should not be exceeded in these patients.

As with all medications, the lowest effective dose should be used.

HOW SUPPLIED

Triazolam tablets are available in the following strengths and package sizes:

0.125 mg (white, imprinted G3717):
Bottles of 10 | NDC 59762-3717-4
Bottles of 100 | NDC 59762-3717-9
0.25 mg (powder blue, scored, imprinted G3718):
Bottles of 10 | NDC 59762-3718-4
Bottles of 100 | NDC 59762-3718-9
Bottles of 500 | NDC 59762-3718-3

STORAGE AND HANDLING

Store at controlled room temperature 20° to 25°C (68° to 77°F) [see USP].

LAB-0689-5.0
January 2017

MEDICATION GUIDE
TRIAZOLAM Tablets, C-IV

What is the most important information I should know about triazolam?

- Triazolam is a benzodiazepine medicine. Taking benzodiazepines with opioid medicines, alcohol, or other central nervous system depressants (including street drugs) can cause severe drowsiness, breathing problems (respiratory depression), coma and death.
- After taking triazolam, you may get up out of bed while not being fully awake and do an activity that you do not know you are doing. The next morning, you may not remember that you did anything during the night. You have a higher chance for doing these activities if you drink alcohol or take other medicines that make you sleepy with triazolam. Reported activities include:
  - driving a car ("sleep-driving")
  - making and eating food
  - talking on the phone
  - having sex
  - sleep-walking
  Call your healthcare provider right away if you find out that you have done any of the above activities after taking triazolam.
- Do not take triazolam unless you are able to stay in bed a full night (7 to 8 hours) before you must be active again.
- Do not take more triazolam than prescribed.

What is triazolam?

- Triazolam is a prescription medicine used to treat certain types of insomnia including difficulty falling asleep, waking up often during the night, or waking up early in the morning.
- Triazolam is a federal controlled substance (C-IV) because it can be abused or lead to dependence. Keep triazolam in a safe place to prevent misuse and abuse. Selling or giving away triazolam may harm others, and is against the law. Tell your healthcare provider if you have ever abused or been dependent on alcohol, prescription medicines or street drugs.
- It is not known if triazolam is safe and effective in children.
- Elderly patients are especially susceptible to dose related adverse effects when taking triazolam.
- It is not known if triazolam is safe and effective for use longer than 2 to 3 weeks.

Do not take triazolam if you:

- are allergic to triazolam, other benzodiazepines, or any of the ingredients in triazolam. See the end of this Medication Guide for a complete list of ingredients in triazolam.
- take antifungal medicines including ketoconazole and itraconazole
- take a medicine to treat depression called nefazodone
- take medicines to treat HIV infection called protease inhibitors, including ritonavir, indinavir, nelfinavir, saquinavir or lopinavir

Before you take triazolam, tell your healthcare provider about all of your medical conditions, including if you:

- have a history of depression, mental illness or, suicidal thoughts
- have a history of drug or alcohol abuse or addiction
- have kidney or liver disease
- have lung disease, breathing problems, or sleep apnea
- are pregnant or plan to become pregnant. Triazolam may harm your unborn baby.
- are breastfeeding or plan to breastfeed. It is not known if triazolam can pass through your breast milk. Talk to your healthcare provider about the best way to feed your baby if you take triazolam.

Tell your healthcare provider about all of the medicines you take, including prescription and over-the-counter medicines, vitamins, and herbal supplements. Do not take triazolam with other medicines that can make you sleepy. Taking triazolam with certain other medicines can cause side effects or affect how well triazolam or the other medicines work. Do not start or stop other medicines without talking to your healthcare provider.

How should I take triazolam?

- See "What is the most important information I should know about triazolam?"
- Take triazolam exactly as your healthcare provider tells you to take it.
- Take triazolam right before you get into bed. Or you can take triazolam after you have been in bed and have trouble falling asleep.
- Do not take triazolam with or right after a meal.
- Do not take triazolam unless you are able to get a full night's sleep before you must be active again.
- If you take too much triazolam, get emergency treatment right away

What should I avoid while taking triazolam?

- Do not drive, operate machinery, do other dangerous activities or do anything that needs you to be alert until you know how triazolam affects you.
- You should not drink alcohol while you are taking triazolam.

What are the possible side effects of triazolam?
Triazolam may cause serious side effects, including:

- See "What is the most important information I should know about triazolam?"
- Other conditions. Call your healthcare provider if your insomnia worsens or is not better within 7 to 10 days. This may mean that there is another condition causing your sleep problem.
- Abnormal thoughts and behavior. Symptoms include more outgoing or aggressive behavior than normal, confusion, agitation, hallucinations, worsening of depression, and suicidal thoughts or actions.
- Withdrawal symptoms. You may have withdrawal symptoms for 1 to 2 days when you stop taking triazolam suddenly. Withdrawal symptoms include trouble sleeping, unpleasant feelings, stomach and muscle cramps, vomiting, sweating, shakiness, and seizures. Talk to your healthcare provider about slowly stopping triazolam to avoid withdrawal symptoms.
- Abuse and dependence. Taking triazolam can cause physical and psychological dependence. Physical and psychological dependence is not the same as drug addiction. Your healthcare provider can tell you more about the differences between physical and psychological dependence and drug addiction.
- Memory loss, including "traveler's amnesia"
- Anxiety
- Severe allergic reactions. Symptoms include swelling of the tongue or throat, trouble breathing, nausea and vomiting. Get emergency medical help if you have these symptoms after taking triazolam.

The most common side effects of triazolam include:

- drowsiness
- dizziness
- "pins and needles" feeling on your skin

- headache
- lightheadedness
- difficulty with coordination

You may still feel drowsy the next day after taking triazolam. Do not drive or do other dangerous activities (including operating machinery) after taking triazolam until you feel fully awake.
These are not all the possible side effects of triazolam. Call your doctor for medical advice about side effects. You may report side effects to FDA at 1-800-FDA-1088.

How should I store triazolam?

- Store at room temperature between 68°F to 77° F (20°C to 25°C).
- Protect from light.
- Keep triazolam and all medicines out of the reach of children
- Do not use triazolam after the expiration date on the bottle.

General information about the safe and effective use of triazolam.

- Medicines are sometimes prescribed for purposes other than those listed in a Medication Guide.
- Do not use triazolam for a condition for which it was not prescribed.
- Do not give triazolam to other people, even if they have the same symptoms that you have. It may harm them.
- You can ask your healthcare provider or pharmacist for information about triazolam that is written for healthcare professionals.

What are the ingredients in triazolam?
Active Ingredient: triazolam
Inactive Ingredients: 0.125 mg tablet: cellulose, corn starch, docusate sodium, lactose, magnesium stearate, silicon dioxide, sodium benzoate, 0.25 mg tablet: cellulose, corn starch, docusate sodium, FD&C Blue No. 2, lactose, magnesium stearate, silicon dioxide, sodium benzoate.

Rx only

This Medication Guide has been approved by the U.S. Food and Drug Administration.

This product's label may have been updated. For current full prescribing information, please visit www.greenstonellc.com.

LAB-0260-10.0
January 2017

Repackaging Information

Please reference the How Supplied section listed above for a description of individual tablets. This drug product has been received by Aphena Pharma - TN in a manufacturer or distributor packaged configuration and repackaged in full compliance with all applicable cGMP regulations. The package configurations available from Aphena are listed below:

Count | 0.25 mg
30 | 43353-451-30
60 | 43353-451-53

Store between 20°-25°C (68°-77°F). See USP Controlled Room Temperature. Dispense in a tight light-resistant container as defined by USP. Keep this and all drugs out of the reach of children.

Repackaged by:
Cookeville, TN 38506
20171116JH

PRINCIPAL DISPLAY PANEL - 0.25 mg

NDC 43353-451 - Triazolam 0.25 mg - Rx Only